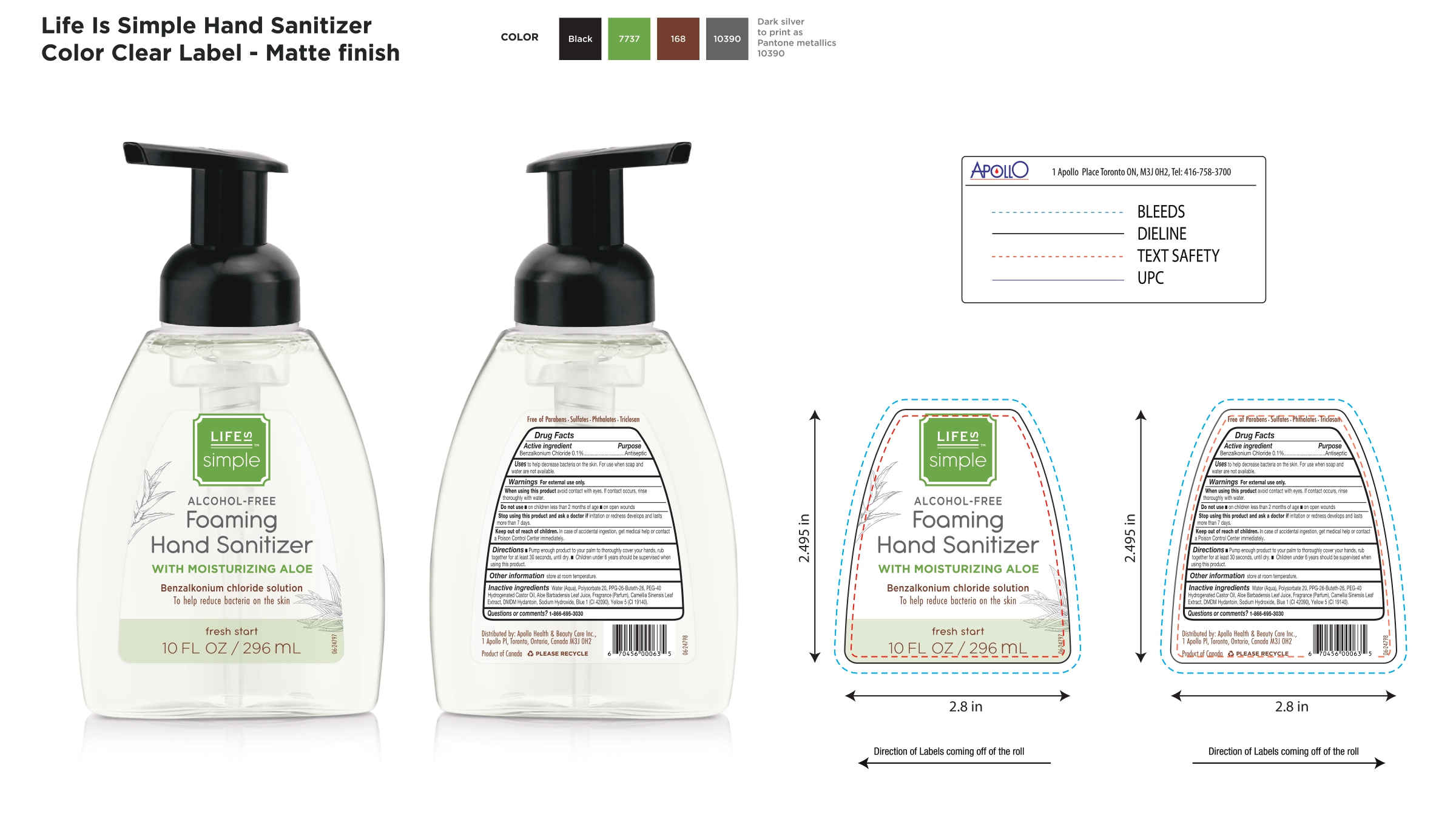 DRUG LABEL: Life is Simple Hand Sanitizer
NDC: 63148-500 | Form: AEROSOL, FOAM
Manufacturer: Apollo Health and Beauty Care Inc
Category: otc | Type: HUMAN OTC DRUG LABEL
Date: 20250206

ACTIVE INGREDIENTS: BENZALKONIUM CHLORIDE 1 mg/1 mL
INACTIVE INGREDIENTS: CAMELLIA SINENSIS LEAF; PEG-40 HYDROGENATED CASTOR OIL; FRAGRANCE CLEAN ORC0600327; POLYSORBATE 20; PPG-26-BUTETH-26; ALOE VERA LEAF; DMDM HYDANTOIN; SODIUM HYDROXIDE; FD&C BLUE NO. 1; FD&C YELLOW NO. 5; WATER

NDC 63148-500, Life is Simple- Alcohol free Hand Sanitizer

Active Ingredients

Benzalkonium Chloride 0.1%

Purpose

Antiseptic

Uses

To help decrease bacteria on the skin. For use when soap and water are not available.

Warnings

For External use only

When using this product

Avoid contact with eyes. If contact occurs, rinse thoroughly with water.

Do not use

- on children less than 2 months of age.
- on open wounds.

Stop use and ask a doctor

If irritation or redness develops and lasts more than 7 days.

Keep out of reach of children

In case of accidental ingestion, get medical help or contact a Poison Control Centre immedoately

Directions

- Pump enough product to your palm to thoroughly cover your hands, rub together for at least 30 seconds, until dry.
- Children under 6 years should be supervised when using this product.

Other information

- Store at room temperature

Inactive Ingredients

Water, Polysorbate 20, PPG-26-Buteth-26, PEG-40 Hydrogenated Castor Oil, Aloe Barbadensis Leaf Juice, Fragrance (Parfum), Camellia Sinensis Leaf Extract, DMDM Hydantoin, Sodium Hydroxide, Blue 1 (CI 42090), Yellow 5 (CI 19140)

Questions or comments ?

1-866-695-3030